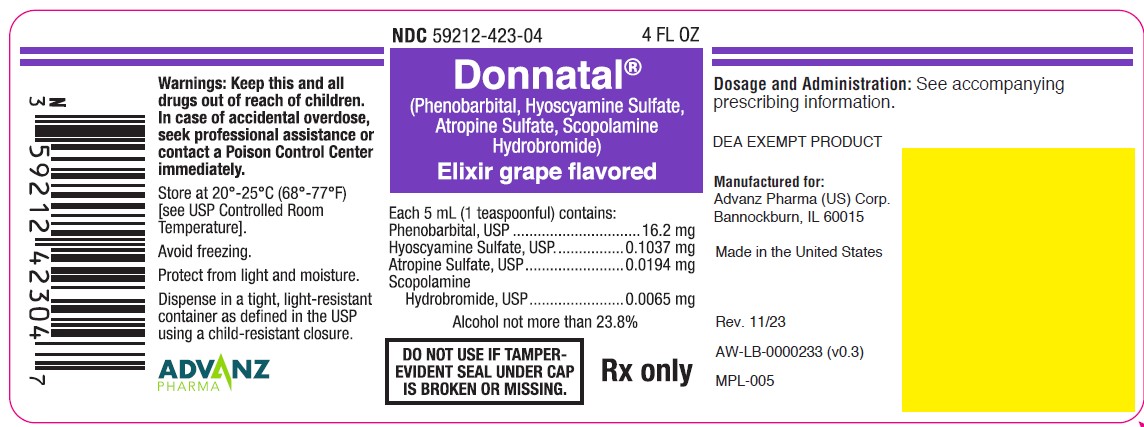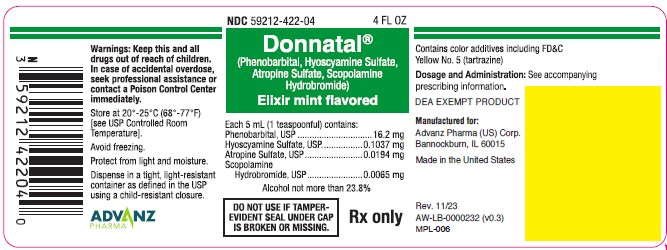 DRUG LABEL: Donnatal
NDC: 59212-423 | Form: ELIXIR
Manufacturer: Advanz Pharma (US) Corp.
Category: prescription | Type: Human Prescription Drug Label
Date: 20241205
DEA Schedule: CIV

ACTIVE INGREDIENTS: Phenobarbital 16.2 mg/5 mL; Hyoscyamine sulfate 0.1037 mg/5 mL; Atropine sulfate 0.0194 mg/5 mL; Scopolamine hydrobromide 0.0065 mg/5 mL
INACTIVE INGREDIENTS: Glycerin; alcohol; water; sorbitol; sucrose; saccharin sodium; FD&C Blue No. 1; FD&C Red No. 3

DONNATAL® (Phenobarbital, Hyoscyamine Sulfate, Atropine Sulfate, Scopolamine Hydrobromide) Elixir
Rx Only
Revised: 11/23

DESCRIPTION

Donnatal® Elixir - Grape

Each 5 mL (teaspoonful) of elixir (alcohol not more than 23.8%) contains:

Phenobarbital, USP.............................. 16.2 mg
Hyoscyamine Sulfate, USP............... 0.1037 mg
Atropine Sulfate, USP...................... 0.0194 mg
Scopolamine Hydrobromide, USP.... 0.0065 mg

Inactive Ingredients

Purified Water, Glycerin, Sorbitol, Ethyl Alcohol, Sucrose, Saccharin Sodium, Artificial and Natural Grape Flavor, FD&C Red #3, and FD&C Blue #1.

DESCRIPTION

Donnatal® Elixir - Mint

Each 5 mL (teaspoonful) of elixir (alcohol not more than 23.8%) contains:

Phenobarbital, USP.............................. 16.2 mg
Hyoscyamine Sulfate, USP............... 0.1037 mg
Atropine Sulfate, USP...................... 0.0194 mg
Scopolamine Hydrobromide, USP.... 0.0065 mg

Inactive Ingredients

Purified Water, Glycerin, Sorbitol, Ethyl Alcohol, Sucrose, Saccharin Sodium, Natural Mint Flavor, FD&C Yellow #5, and FD&C Blue #1.

CLINICAL PHARMACOLOGY

This drug combination provides natural belladonna alkaloids in a specific, fixed ratio combined with phenobarbital to provide peripheral anticholinergic/antispasmodic action and mild sedation.

INDICATIONS AND USAGE

Based on a review of this drug by the National Academy of Sciences-National Research Council and/or other information, FDA has classified the indications as follows: "Possibly" effective: For use as adjunctive therapy in the treatment of irritable bowel syndrome (irritable colon, spastic colon, mucous colitis) and acute enterocolitis.
May also be useful as adjunctive therapy in the treatment of duodenal ulcer.
Final classification of the less-than-effective indications requires further investigation.
IT HAS NOT BEEN SHOWN CONCLUSIVELY WHETHER ANTICHOLINERGIC/ANTISPASMODIC DRUGS AID IN THE HEALING OF A DUODENAL ULCER, DECREASE THE RATE OF RECURRENCES OR PREVENT COMPLICATIONS.

CONTRAINDICATIONS

- glaucoma;
- obstructive uropathy (for example, bladder neck obstruction due to prostatic hypertrophy);
- obstructive disease of the gastrointestinal tract (as in achalasia, pyloroduodenal stenosis, etc.);
- paralytic ileus, intestinal atony of the elderly or debilitated patient;
- unstable cardiovascular status in acute hemorrhage;
- severe ulcerative colitis especially if complicated by toxic megacolon;
- myasthenia gravis;
- hiatal hernia associated with reflux esophagitis;
- in patients with known hypersensitivity to any of the ingredients.

Phenobarbital is contraindicated in acute intermittent porphyria and in those patients in whom phenobarbital produces restlessness and/or excitement.

WARNINGS

Donnatal® Elixir can cause fetal harm when administered to a pregnant woman. Animal reproduction studies have not been conducted with Donnatal® Elixir. If this drug is used during pregnancy, or if the patient becomes pregnant while taking this drug, the patient should be apprised of the potential hazard to the fetus.

In the presence of a high environmental temperature, heat prostration can occur with belladonna alkaloids (fever and heatstroke due to decreased sweating).

Diarrhea may be an early symptom of incomplete intestinal obstruction, especially in patients with ileostomy or colostomy. In this instance, treatment with this drug would be inappropriate and possibly harmful.

Donnatal® Elixir may produce drowsiness or blurred vision. The patient should be warned, should these occur, not to engage in activities requiring mental alertness, such as operating a motor vehicle or other machinery, and not to perform hazardous work.

Phenobarbital may decrease the effect of anticoagulants, and necessitate larger doses of the anticoagulant for optimal effect. When the phenobarbital is discontinued, the dose of the anticoagulant may have to be decreased.

Phenobarbital may be habit forming and should not be administered to individuals known to be addiction prone or to those with a history of physical and/or psychological dependence upon drugs.

Since barbiturates are metabolized in the liver, they should be used with caution and initial doses should be small in patients with hepatic dysfunction.

PRECAUTIONS

General

Use with caution in patients with:

- autonomic neuropathy
- hepatic or renal disease
- hyperthyroidism
- coronary heart disease
- congestive heart failure
- cardiac arrhythmias
- tachycardia
- hypertension

Belladonna alkaloids may produce a delay in gastric emptying (antral stasis) which would complicate the management of gastric ulcer.

Do not rely on the use of the drug in the presence of complication of biliary tract disease.

Theoretically, with overdosage, a curare-like action may occur.

Donnatal® Elixir – Mint contains FD&C Yellow No. 5 (tartrazine) which may cause allergic-type reactions (including bronchial asthma) in certain susceptible persons. Although the overall incidence of FD&C Yellow No. 5 (tartrazine) sensitivity in the general population is low, it is frequently seen in patients who also have aspirin hypersensitivity.

Information for Patients

Donnatal® Elixir may produce drowsiness or blurred vision. The patient should be warned, should these occur, not to engage in activities requiring mental alertness, such as operating a motor vehicle or other machinery, and not to perform hazardous work.

Drug Interactions

Phenobarbital may decrease the effect of anticoagulants, and necessitate larger doses of the anticoagulant for optimal effect. When the phenobarbital is discontinued, the dose of the anticoagulant may have to be decreased.

Carcinogenesis, Mutagenesis, Impairment of Fertility

Long-term studies in animals have not been performed to evaluate carcinogenic potential.

Pregnancy

Animal reproduction studies have not been conducted with Donnatal® Elixir. There is positive evidence of human fetal risk based on adverse reaction data from investigational or marketing experience or studies in humans, but potential benefits may warrant use of the drug in pregnant women despite potential risks (see WARNINGS).

Nursing Mothers

It is not known whether this drug is excreted in human milk. Because many drugs are excreted in human milk, caution should be exercised when Donnatal® Elixir is administered to a nursing woman.

Geriatric Use

Elderly patients may react with symptoms of excitement, agitation, drowsiness, and other untoward manifestations to even small doses of the drug.

ADVERSE REACTIONS

Adverse reactions may include xerostomia; urinary hesitancy and retention; blurred vision; tachycardia; palpitation; mydriasis; cycloplegia; increased ocular tension; loss of taste sense; headache; nervousness; drowsiness; weakness; dizziness; insomnia; nausea; vomiting; impotence; suppression of lactation; constipation; bloated feeling; musculoskeletal pain; severe allergic reaction or drug idiosyncrasies, including anaphylaxis, urticaria, and other dermal manifestations; and decreased sweating.

Acquired hypersensitivity to barbiturates consists chiefly in allergic reactions that occur especially in persons who tend to have asthma, urticaria, angioedema, and similar conditions. Hypersensitivity reactions in this category include localized swelling, particularly of the eyelids, cheeks, or lips, and erythematous dermatitis. Rarely, exfoliative dermatitis (e.g. Stevens-Johnson syndrome and toxic epidermal necrolysis) may be caused by phenobarbital and can prove fatal. The skin eruption may be associated with fever, delirium, and marked degenerative changes in the liver and other parenchymatous organs. In a few cases, megaloblastic anemia has been associated with the chronic use of phenobarbital.

Phenobarbital may produce excitement in some patients, rather than a sedative effect.

To report SUSPECTED ADVERSE REACTIONS, contact Advanz Pharma (US) Corp. at 1-877-370-1142 or FDA at 1-800-FDA-1088 or www.fda.gov/medwatch.

DRUG ABUSE AND DEPENDENCE

Abuse

Phenobarbital may be habit forming and should not be administered to individuals known to be addiction prone or to those with a history of physical and/or psychological dependence upon drugs (see WARNINGS).

Dependence

In patients habituated to barbiturates, abrupt withdrawal may produce delirium or convulsions.

OVERDOSAGE

The signs and symptoms of overdose are headache, nausea, vomiting, blurred vision, dilated pupils, hot and dry skin, dizziness, dryness of the mouth, difficulty in swallowing, and CNS stimulation. Treatment should consist of gastric lavage, emetics, and activated charcoal. If indicated, parenteral cholinergic agents such as physostigmine or bethanechol chloride should be used.

DOSAGE AND ADMINISTRATION

The dosage of Donnatal® Elixir should be adjusted to the needs of the individual patient to assure symptomatic control with a minimum of adverse effects.

Donnatal® Elixir. Adults: One or two teaspoonfuls of elixir three or four times a day according to conditions and severity of symptoms.

Pediatric patients: may be dosed every 4 to 6 hours. Use a pediatric dosing device or oral syringe to measure the dose.

Starting Dosage
Body weight | Every 4 hours | Every 6 hours
10 lb. (4.5 kg) | 0.5 mL | 0.75 mL
20 lb. (9.1 kg) | 1 mL | 1.5 mL
30 lb. (13.6 kg) | 1.5 mL | 2 mL
50 lb. (22.7 kg) | 2.5 mL | 3.75 mL
75 lb. (34 kg) | 3.75 mL | 5 mL
100 lb. (45.4 kg) | 5 mL | 7.5 mL

HOW SUPPLIED

Donnatal® Elixir - Grape is a purple colored, grape flavored liquid.

- 4 fl oz (118 mL) bottles- NDC 59212-423-04.
- 1 Pint (473 mL) bottles- NDC 59212-423-16.

Donnatal® Elixir - Mint is a green colored, mint flavored liquid.

- 4 fl oz (118 mL) bottles- NDC 59212-422-04.
- 1 Pint (473 mL) bottles- NDC 59212-422-16.

Avoid Freezing

Store Donnatal® Elixir at 20º- 25ºC (68º - 77ºF) [see USP Controlled Room Temperature]. Protect from light and moisture.

Dispense in a tight, light-resistant container as defined in the USP using a child-resistant closure.

DEA EXEMPT PRODUCT

Manufactured for:
Advanz Pharma (US) Corp.
Bannockburn, IL 60015

DONNATAL® is a registered trademark of Mercury Pharma Group Limited.
Distributed by Advanz Pharma (US) Corp. under license.

Revised:11/23

Principal Display Panel - Donnatal Elixir - Grape, 4 oz

NDC 59212-423-04 4 FL OZ

Donnatal®
(Phenobarbital, Hyoscyamine Sulfate, Atropine Sulfate, Scopolamine Hydrobromide)

Elixir grape flavored

Each 5 mL (1 teaspoonful) contains:

Phenobarbital, USP.............................. 16.2 mg
Hyoscyamine Sulfate, USP............... 0.1037 mg
Atropine Sulfate, USP...................... 0.0194 mg
Scopolamine Hydrobromide, USP.... 0.0065 mg

Alcohol not more than 23.8%

DO NOT USE IF TAMPER-EVIDENT SEAL UNDER CAP IS BROKEN OR MISSING.

Rx only

Principal Display Panel - Donnatal Elixir - Mint, 4 oz

NDC 59212-422-04 4 FL OZ

Donnatal®
(Phenobarbital, Hyoscyamine Sulfate, Atropine Sulfate, Scopolamine Hydrobromide)

Elixir mint flavored

Each 5 mL (1 teaspoonful) contains:

Phenobarbital, USP.............................. 16.2 mg
Hyoscyamine Sulfate, USP............... 0.1037 mg
Atropine Sulfate, USP...................... 0.0194 mg
Scopolamine Hydrobromide, USP.... 0.0065 mg

Alcohol not more than 23.8%

DO NOT USE IF TAMPER-EVIDENT SEAL UNDER CAP IS BROKEN OR MISSING.

Rx only